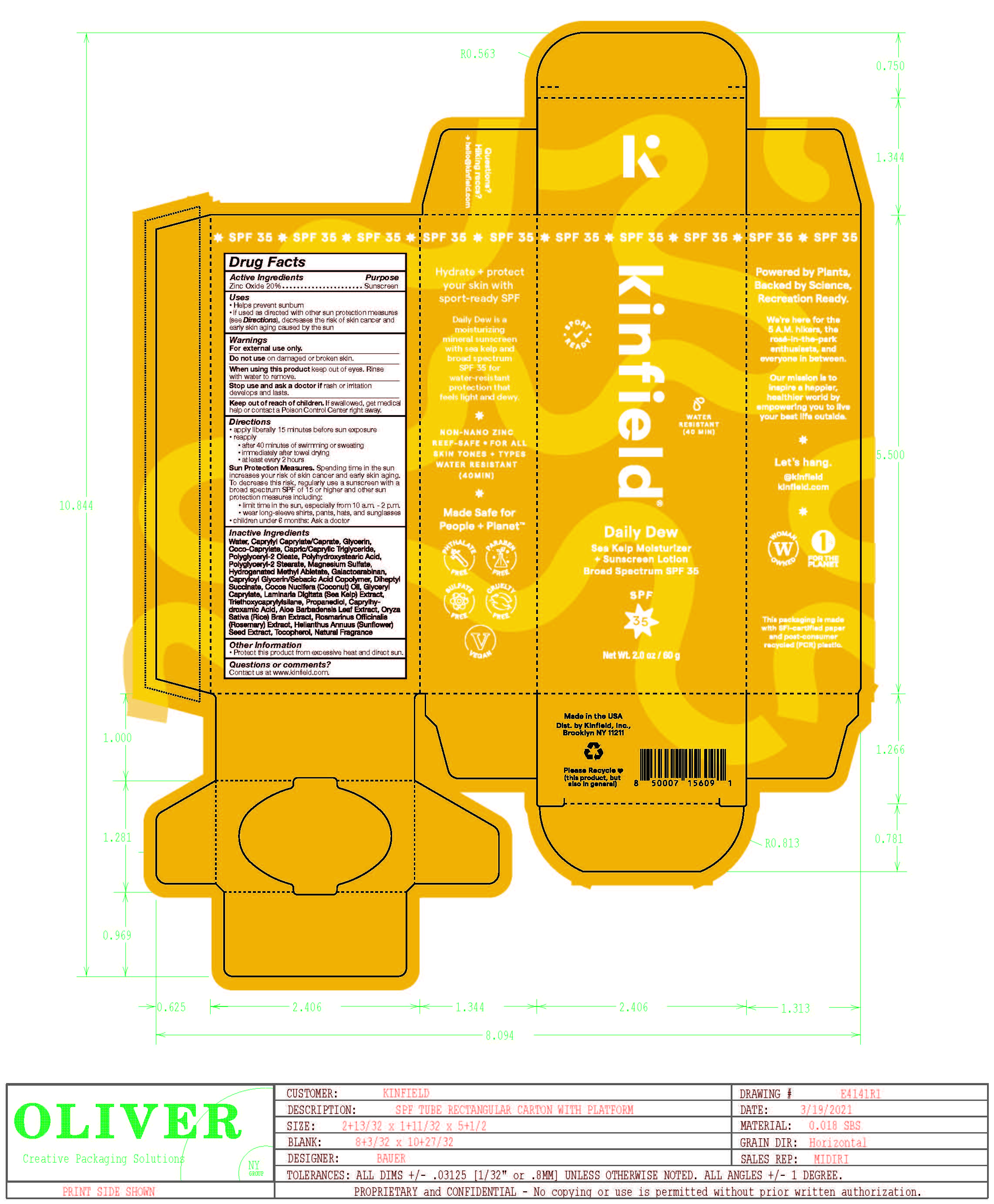 DRUG LABEL: Kinfield Daily Dew Sea Kelp Moisturizer Sunscreen Broad Spectrum SPF 35
NDC: 81750-010 | Form: LOTION
Manufacturer: Kinfield, Inc.
Category: otc | Type: HUMAN OTC DRUG LABEL
Date: 20251230

ACTIVE INGREDIENTS: ZINC OXIDE 20 g/100 g
INACTIVE INGREDIENTS: GLYCERYL CAPRYLATE; LAMINARIA DIGITATA; TRIETHOXYCAPRYLYLSILANE; PROPANEDIOL; CAPRYLHYDROXAMIC ACID; ALOE VERA LEAF; WATER; CAPRYLYL CAPRYLATE/CAPRATE; GLYCERIN; COCO-CAPRYLATE; POLYGLYCERYL-2 OLEATE; POLYGLYCERYL-2 STEARATE; POLYHYDROXYSTEARIC ACID (2300 MW); MAGNESIUM SULFATE ANHYDROUS; HYDROGENATED METHYL ABIETATE; GALACTOARABINAN; CAPRYLOYL GLYCERIN/SEBACIC ACID COPOLYMER (2000 MPA.S); DIHEPTYL SUCCINATE; COCOS NUCIFERA WHOLE; ORYZA SATIVA WHOLE; ROSMARINUS OFFICINALIS FLOWER; HELIANTHUS ANNUUS WHOLE; TOCOPHEROL

DRUG FACTS

Active Ingredients

Zinc Oxide 20%

Uses

• helps prevent sunburn • if used as directed with other
sun protection measures (see Directions), decreases the
risk of skin cancer and early skin aging caused by the sun

Warnings

For external use only
Do not use on damaged or broken skin.
When using this product keep out of eyes. Rinse with water to remove.
Stop use and ask a docor if rash occurs
Keep out of reach of children. If swalled, get medical help or contact a Poison Control Center right away.

Directions

• apply generously 15 minutes before sun exposure
• reapply: •after 40 minutes of swimming or sweating
• immediately after towel drying • at least every 2 hours

• Sun Protection Measures. Spending time in the sun
increases your risk of skin cancer and early skin aging. To decrease
this risk, regularly use a sunscreen with a Broad Spectrum SPF
value of 15 or higher and other sun protection measures including:
• limit time in the sun, especially from 10 a.m. - 2 p.m.
• wear long-sleeved shirts, pants, hats, and sunglasses
• children under 6 months of age: Ask a doctor

Inactive ingredients

Water, Capylyl Caprylate/Caprate, Glycerin, Coco-Caprylate, Capric/Caprylic Triglyceride, Polyglycerl-2-Oleate, Polyhydroxystearic Acid, Polyglycerl-2 Stearate, Magnesium Sulfate, Hydrogenated Methyl Abietate, Galactoarabinan, Capryloyl Glycerin/Sebacic Acid Copolymer, Diheptyl Succinate, Cocos Nucifera (Coconut) Oil, Glyceryl Caprylate, Laminaria Digitata Extract, Triethoxycaprylylsilane, Propanediol, Caprylhydroxamic Acid, Aloe Barbadensis Leaf Extract, Oryza Sativa Bran Extract, Rosmarinus Officinalis Extract, Helianthus Annuus Seed Extract, Tocopherol, Natural Fragrance

Other Information

• protect the product in this container from excessive
heat and direct sun

Questions or Comments?

Conctact us at www.kinfield.com

Purpose

Purpose: Sunscreen

Keep out of reach of children. If product is swallowed, get medical help or contact a Poison Control Center right away.